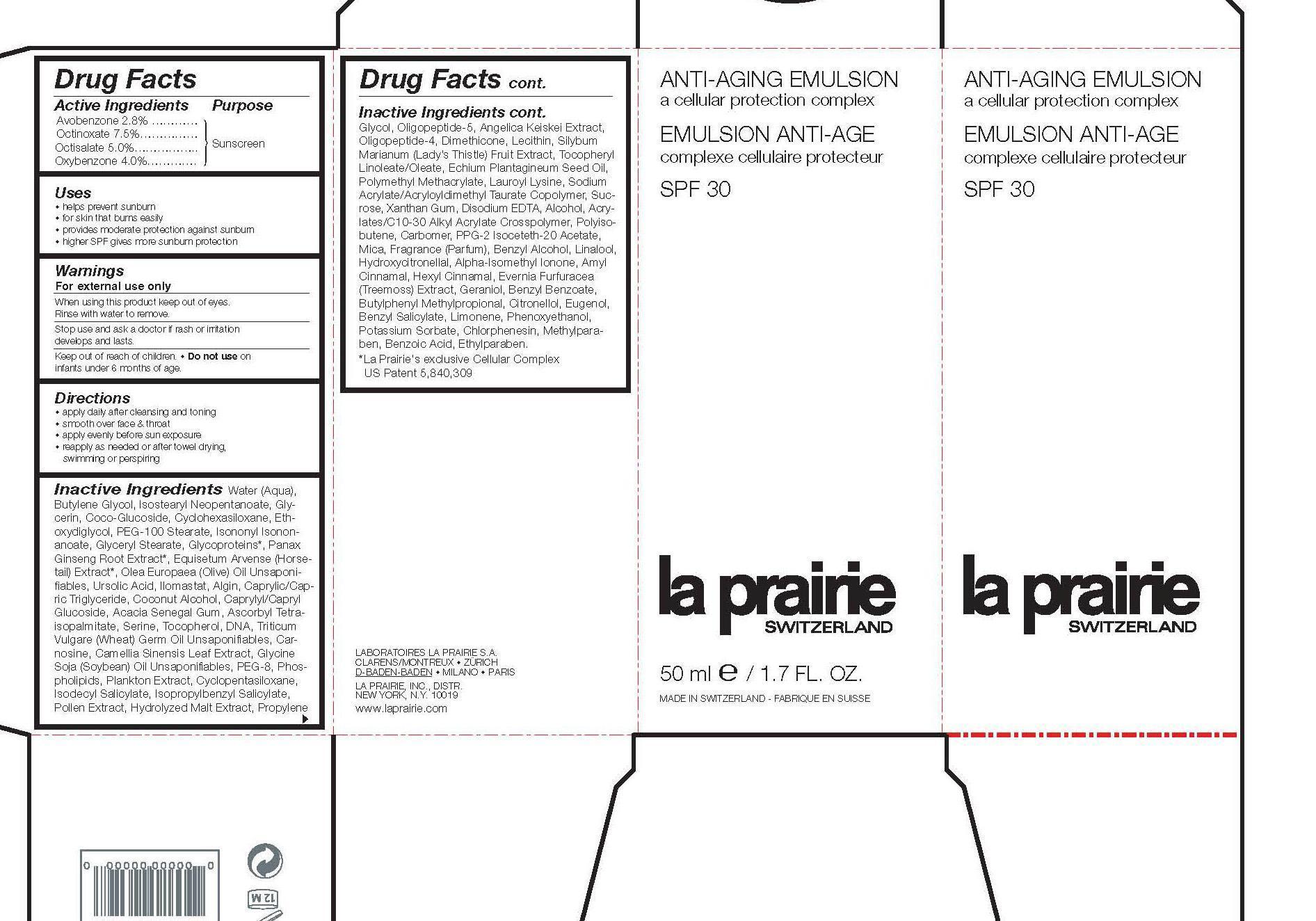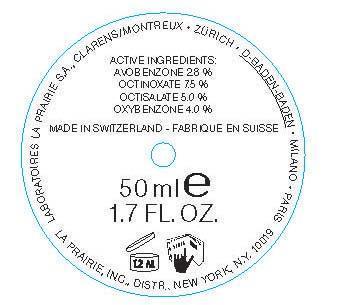 DRUG LABEL: Anti-Aging Emulsion
NDC: 68807-304 | Form: CREAM
Manufacturer: Temmentec AG
Category: otc | Type: HUMAN OTC DRUG LABEL
Date: 20170103

ACTIVE INGREDIENTS: Avobenzone 2.8 g/100 mL; Octinoxate 7.5 g/100 mL; Octisalate 5 g/100 mL; OXYBENZONE 4 g/100 mL
INACTIVE INGREDIENTS: WATER; BUTYLENE GLYCOL; GLYCERIN; COCO GLUCOSIDE; CYCLOMETHICONE 6; DIETHYLENE GLYCOL MONOETHYL ETHER; PEG-100 STEARATE; GLYCERYL MONOSTEARATE; PANAX GINSENG ROOT WATER; EQUISETUM ARVENSE TOP; URSOLIC ACID; CAPRYLIC/CAPRIC ACID; ACACIA; SERINE; CARNOSINE; BANCHA TEA LEAF/TWIG; SOYBEAN OIL; POLYETHYLENE GLYCOL 400; CYCLOMETHICONE 5; PROPYLENE GLYCOL; DIMETHICONE; MILK THISTLE; ECHIUM PLANTAGINEUM SEED OIL; SUCROSE; XANTHAN GUM; CARBOMER INTERPOLYMER TYPE A (ALLYL SUCROSE CROSSLINKED); POLYISOBUTYLENE (35000 MW); CARBOMER 934; MICA; BENZYL ALCOHOL; LINALOOL, (+/-)-; HYDROXYCITRONELLAL; .ALPHA.-AMYLCINNAMALDEHYDE; GERANIOL; BENZYL BENZOATE; BUTYLPHENYL METHYLPROPIONAL; CITRONELLAL; EUGENOL; BENZYL SALICYLATE; LIMONENE, (+)-; PHENOXYETHANOL; POTASSIUM SORBATE; CHLORPHENESIN; METHYLPARABEN; ETHYLPARABEN

Anti-Aging Emulsion SPF 30

Active Ingredients Purpose
Avobenzone 2.7% Sunscreen
Octinoxate 7.5% Sunscreen
Octisalate 5.0% Sunscreen
Oxybenzone 4.0% Sunscreen

PURPOSE

-helps prevent sunburn
-for skin that burns easily
-provides moderate protection against sunburn
-higher SPF gives more sunburn protection

keep out of reach of children

INDICATIONS AND USAGE

-For external use only

-When using this product keep out of eyes
-Rinse with water to remove
-Stop use and ask a doctor if rash or irritation develops and lasts
-Do not use on infants under 6 months.

DOSAGE AND ADMINISTRATION

-apply daily after cleansing and toning
-smooth over face and throat
-apply evenly before sun exposure
-reapply as needed or after towel drying, swimming or perspiring

INACTIVE INGREDIENT

Inactive Ingredients: Water (Aqua), Butylene Glycol, Isostearyl Neopentanoate, Glycerin, Coco-Glucoside, Cyclohexasiloxane, Ethoxydiglycol, PEG-100 Stearate, Isononyl Isononanoate, Glyceryl Stearate, Glycoproteins, Panax Ginseng Root Extract, Equisetum Arvense (Horsetail) Extract, Olea Europaea (Olive) Oil Unsaponifiables, Ursolic Acid, IIomastat, Algin, Caprylyl/Capric Triglyceride, Coconut Alcohol, Caprylyl/Capryl Glucoside, Acacia Senegal Gum, Ascorbyl Tetraisopalmitate, Serine, Tocopherol, DNA, Triticum Vulgare (Wheat) Germ Oil Unsaponifiables, Carnosine, Camellia Sinensis Leaf Extract, Glycine Soja (Soybean) Oil Unsaponifiables, PEG-8, Phospholipids, Plankton Extract, Cyclopentasiloxane, Isodecyl Salicylate, Isopropylbenzyl Salicylate, Pollen Extract, Hydrolyzed Malt Extract, Propylene Glycol, Oligopeptide-5, Angelica Kelskei Extract, Oligopeptide-4, Dimethicone, Lecithin, Silybum Marlanum (Lady's Thistle) Fruit Extract, Tocopheryl Linoleate/Oleate, Echium Plantagineum Seed Oil, Polymethyl Methacrylate, Lauroyl Lysine, Sodium Acrylate/Acryloyldimethyl Taurate Copolymer, Sucrose, Xanthan Gum, Disodium EDTA, Alcohol, Acrylates/C10-30 Alkyl Acrylate Crosspolymer, Polyisobutene, Carbomer, PPG-2 Isoceteth-20 Acetate, Mica, Fragrance (Parfum), Benzyl Alcohol, Linalool, Hydroxycitronellal, Alpha-Isomethyl Ionone, Amyl Cinnamal, Hexyl Cinnamal, Evernia Furfuracea (Treemoss) Extract, Geraniol, Benzyl Benzoate, Butylphenyl Methylpropional, Citronellol, Eugenol, Benzyl Salicylate, Limonene, Phenoxyethanol, Potassium Sorbate, Chlorophenesin, Methylparaben, Benzoic Acid, Ethylparaben.

PACKAGE LABEL

Anti-Aging Emulsion SPF 30
50 ml / 1.7 FL OZ.